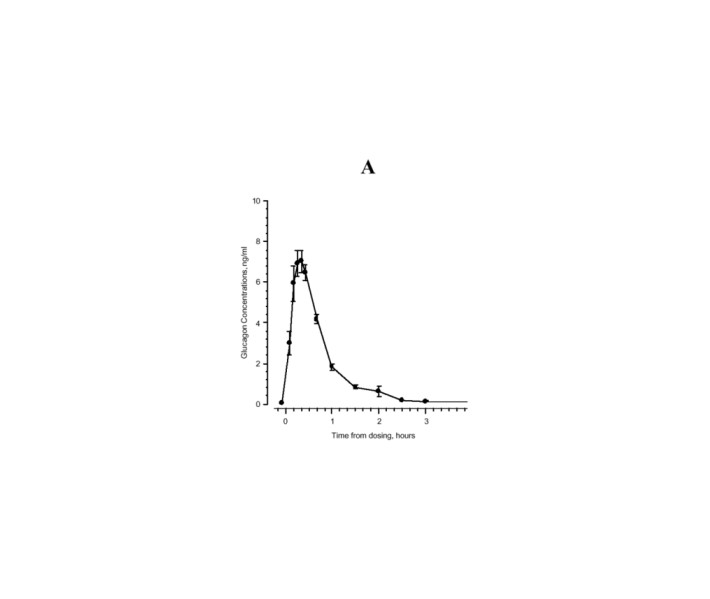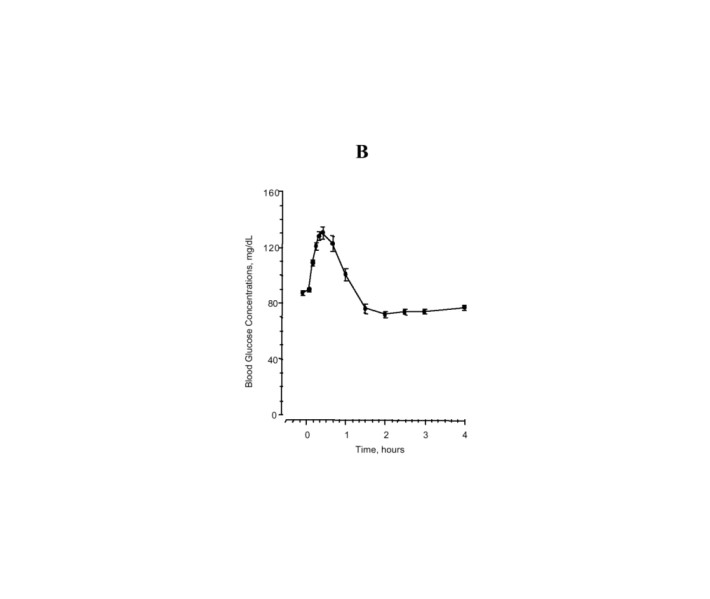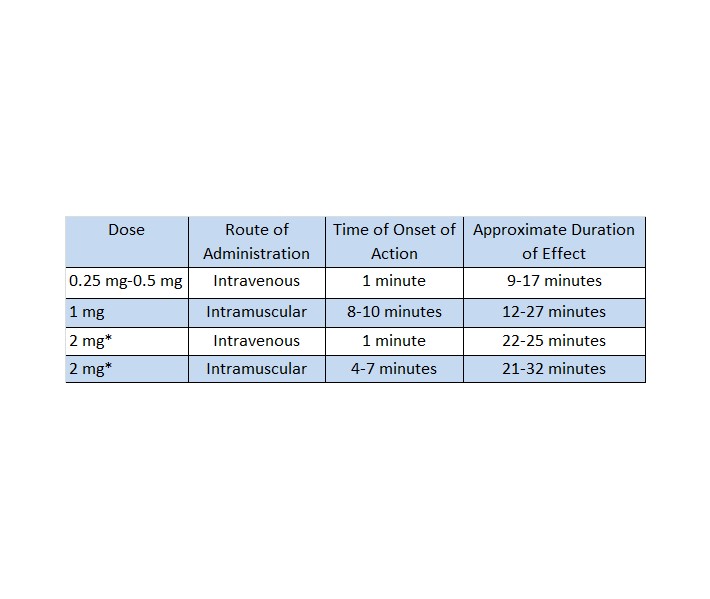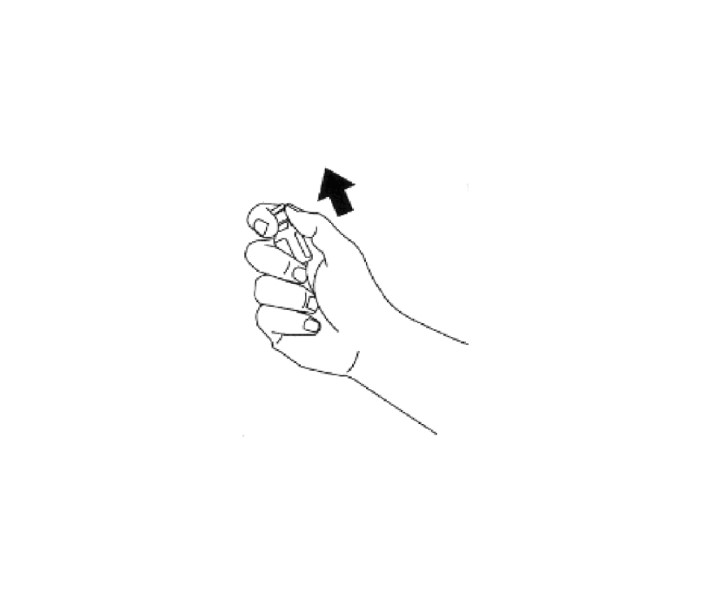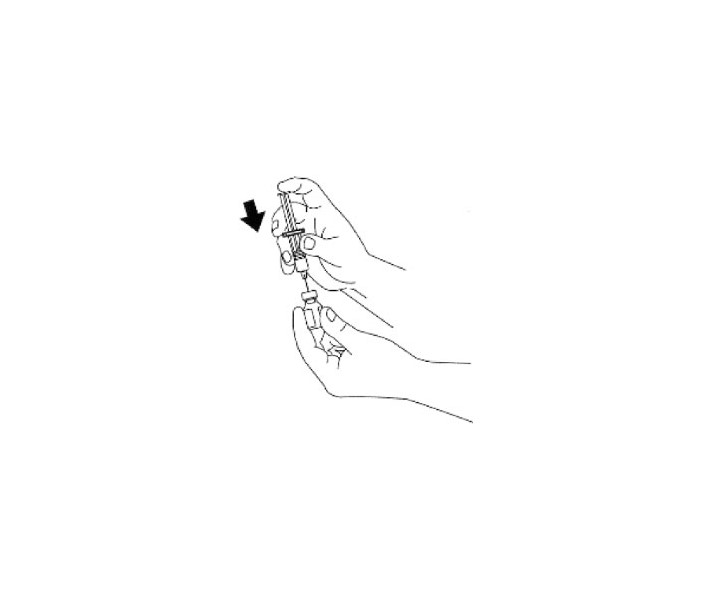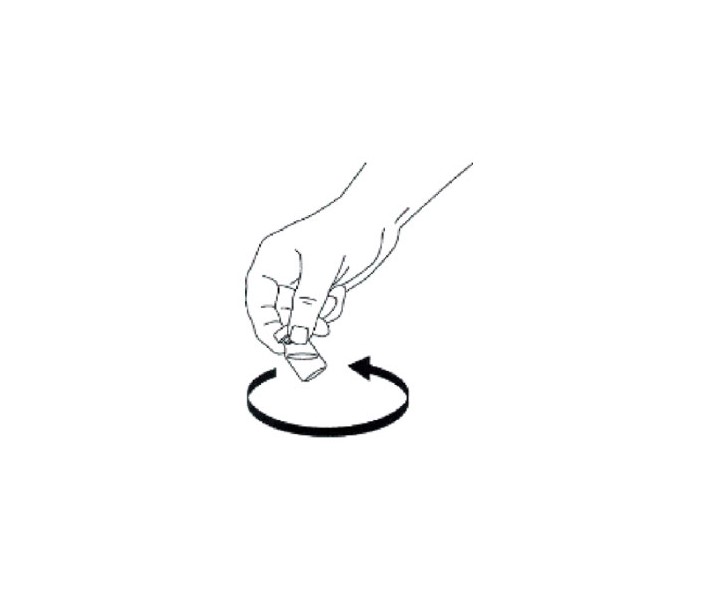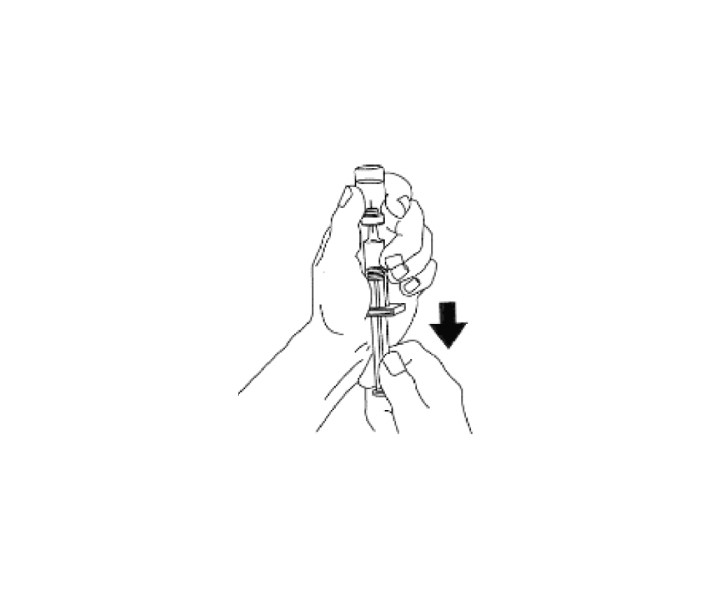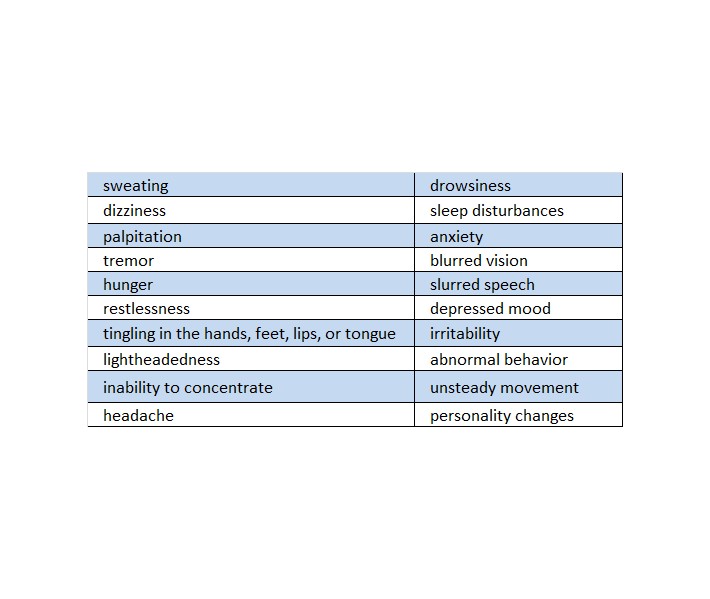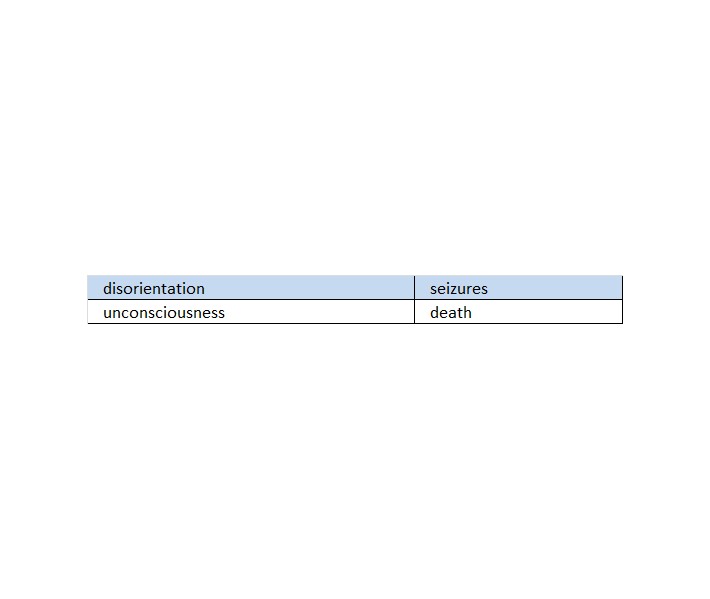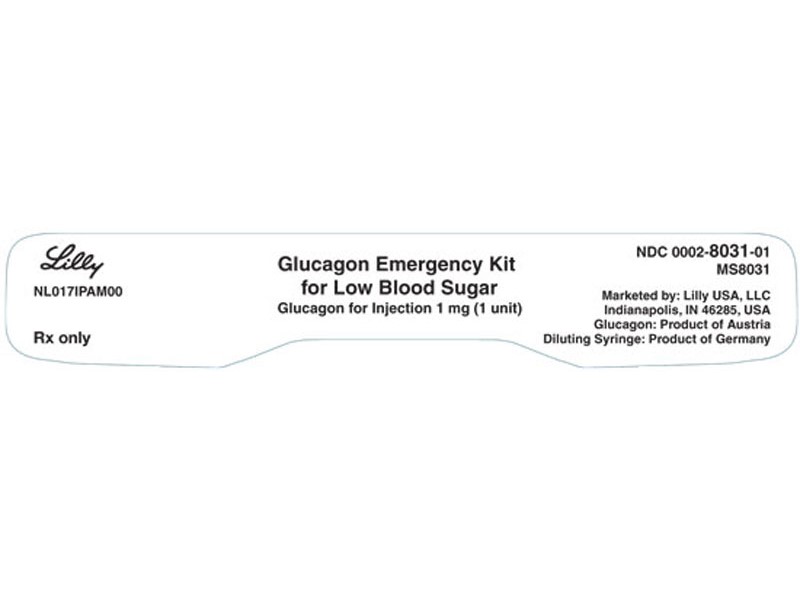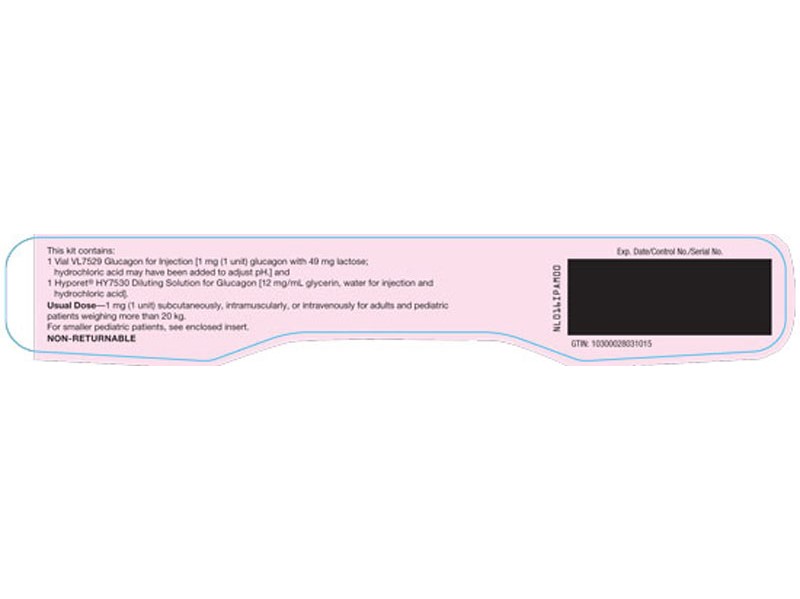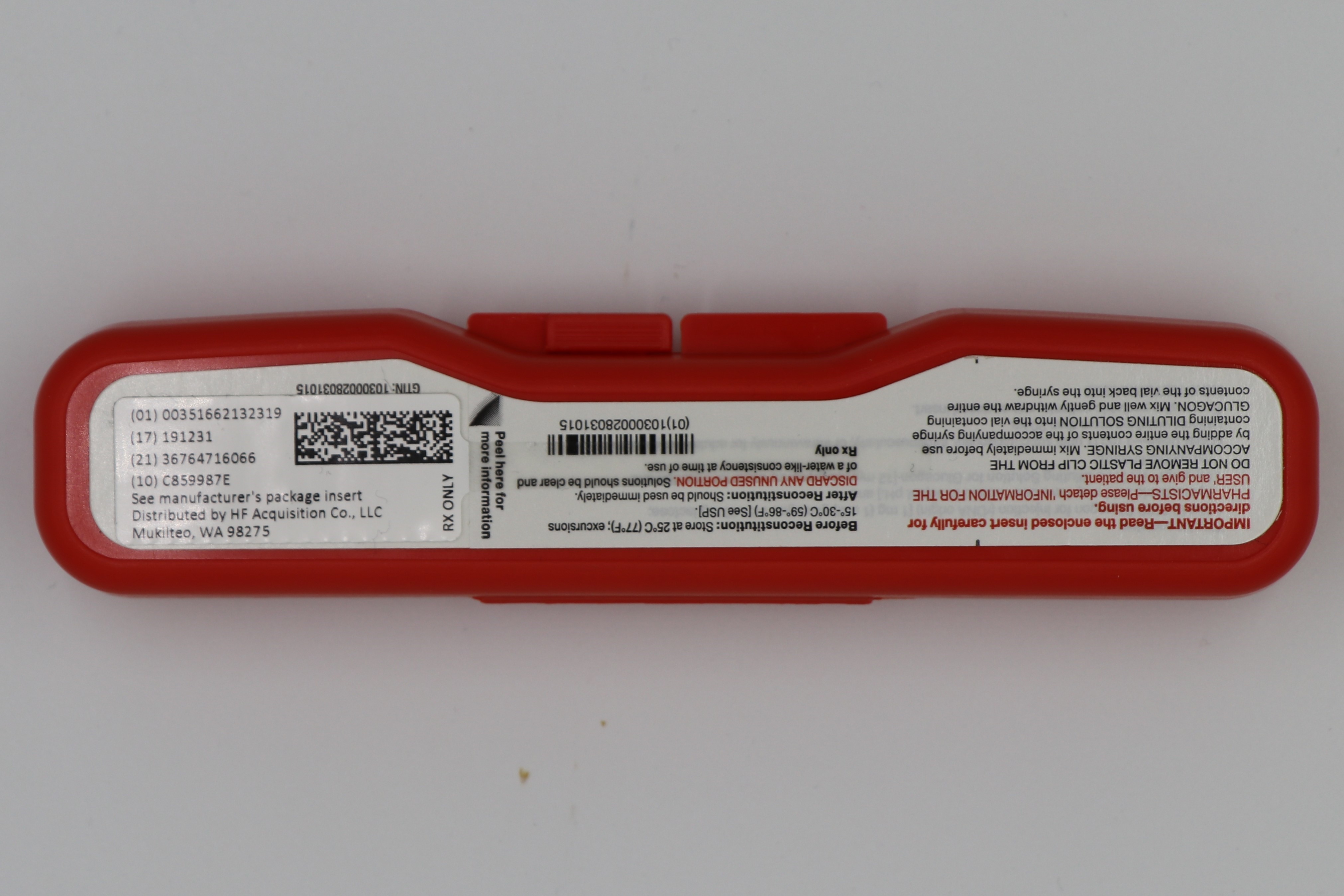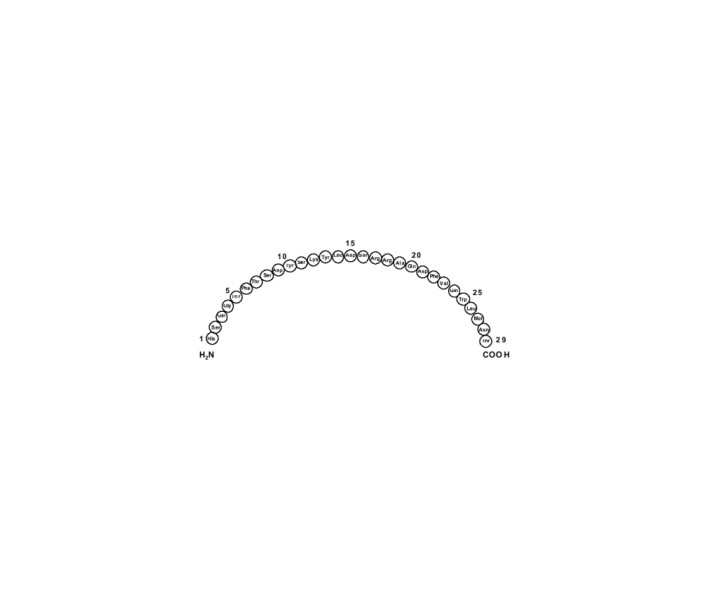 DRUG LABEL: GLUCAG0N
NDC: 51662-1323 | Form: KIT | Route: INTRAVENOUS
Manufacturer: HF Acquisition Co LLC, DBA HealthFirst
Category: prescription | Type: HUMAN PRESCRIPTION DRUG LABEL
Date: 20221209

ACTIVE INGREDIENTS: GLUCAGON 1 mg/1 mL
INACTIVE INGREDIENTS: LACTOSE, UNSPECIFIED FORM 49 mg/1 mL; HYDROCHLORIC ACID; GLYCERIN 12 mg/1 mL; WATER; HYDROCHLORIC ACID

GLUCAGEN(R) {GLUCAGON (rDNA ORGIN) FOR INJECTION} 1mg PER KIT

DESCRIPTION

Glucagon for Injection is a polypeptide hormone identical to human glucagon that increases blood glucose and relaxes smooth muscle of the gastrointestinal tract. Glucagon is synthesized in a special non-pathogenic laboratory strain of Escherichia coli bacteria that has been genetically altered by the addition of the gene for glucagon.

Glucagon is a single-chain polypeptide that contains 29 amino acid residues and has a molecular weight of 3483.

The empirical formula is C153H225N43O49S. The primary sequence of glucagon is shown below.

Crystalline glucagon is a white to off-white powder. It is relatively insoluble in water but is soluble at a pH of less than 3 or more than 9.5.

Glucagon is available for use intravenously, intramuscularly, or subcutaneously in a kit that contains a vial of sterile glucagon and a syringe of sterile diluent. The vial contains 1 mg of glucagon and 49 mg of lactose. Hydrochloric acid may have been added during manufacture to adjust the pH of the glucagon. One International Unit of glucagon is equivalent to 1 mg of glucagon.1 The diluent syringe contains 12 mg/mL of glycerin, Water For Injection, and hydrochloric acid.

CLINICAL PHARMACOLOGY

Glucagon increases blood glucose concentration and is used in the treatment of severe hypoglycemia. Glucagon acts only on liver glycogen, converting it to glucose.

Glucagon administered through a parenteral route relaxes smooth muscle of the stomach, duodenum, small bowel, and colon.

Pharmacokinetics

Glucagon has been studied following intramuscular, subcutaneous, and intravenous administration in adult volunteers. Administration of the intravenous glucagon showed dose proportionality of the pharmacokinetics between 0.25 and 2.0 mg. Calculations from a 1 mg dose showed a small volume of distribution (mean, 0.25 L/kg) and a moderate clearance (mean, 13.5 mL/min/kg). The half-life was short, ranging from 8 to 18 minutes.

Maximum plasma concentrations of 7.9 ng/mL were achieved approximately 20 minutes after subcutaneous administration (see Figure 1A). With intramuscular dosing, maximum plasma concentrations of 6.9 ng/mL were attained approximately 13 minutes after dosing.

Glucagon is extensively degraded in liver, kidney, and plasma. Urinary excretion of intact glucagon has not been measured.

Pharmacodynamics

In a study of 25 volunteers, a subcutaneous dose of 1 mg glucagon resulted in a mean peak glucose concentration of 136 mg/dL 30 minutes after injection (see Figure 1B). Similarly, following intramuscular injection, the mean peak glucose level was 138 mg/dL, which occurred at 26 minutes after injection. No difference in maximum blood glucose concentration between animal-sourced and rDNA glucagon was observed after subcutaneous and intramuscular injection.

Figure 1
Mean (±SE) serum glucagon and blood glucose levels after subcutaneous injection of glucagon (1 mg) in 25 normal volunteers

INDICATIONS & USAGE

For the treatment of severe hypoglycemia:

Glucagon is indicated as a treatment for severe hypoglycemia (low blood sugar) which may occur in patients with diabetes mellitus.

Because patients with type 1 diabetes may have less of an increase in blood glucose levels compared with a stable type 2 patient, supplementary carbohydrate should be given as soon as possible, especially to a pediatric patient.

For use as a diagnostic aid:

Glucagon is indicated as a diagnostic aid in the radiologic examination of the stomach, duodenum, small bowel, and colon when diminished intestinal motility would be advantageous.

Glucagon is as effective for this examination as are the anticholinergic drugs. However, as use of glucagon in combination with anticholinergic drugs may result in increased side effects, the use of glucagon in combination with anticholinergic drugs is not recommended.

CONTRAINDICATIONS

Glucagon is contraindicated in patients with known hypersensitivity to it or in patients with known pheochromocytoma.

WARNINGS

Glucagon should be administered cautiously to patients with a history suggestive of insulinoma, pheochromocytoma, or both. In patients with insulinoma, intravenous administration of glucagon may produce an initial increase in blood glucose; however, because of glucagon's hyperglycemic effect the insulinoma may release insulin and cause subsequent hypoglycemia. A patient developing symptoms of hypoglycemia after a dose of glucagon should be given glucose orally, intravenously, or by gavage, whichever is most appropriate.

Exogenous glucagon also stimulates the release of catecholamines. In the presence of pheochromocytoma, glucagon can cause the tumor to release catecholamines, which may result in a sudden and marked increase in blood pressure. If a patient develops a sudden increase in blood pressure, 5 to 10 mg of phentolamine mesylate may be administered intravenously in an attempt to control the blood pressure.

Generalized allergic reactions, including urticaria, respiratory distress, and hypotension, have been reported in patients who received glucagon by injection.

Necrolytic migratory erythema (NME), a skin rash commonly associated with glucagonomas (glucagon-producing tumors) and characterized by scaly, pruritic erythematous plaques, bullae, and erosions, has been reported postmarketing following continuous glucagon infusion. NME lesions may affect the face, groin, perineum and legs or be more widespread. In the reported cases NME resolved with discontinuation of the glucagon, and treatment with corticosteroids was not effective. Should NME occur, consider whether the benefits of continuous glucagon infusion outweigh the risks.

PRECAUTIONS

General

Glucagon is effective in treating hypoglycemia only if sufficient liver glycogen is present. Because glucagon is of little or no help in states of starvation, adrenal insufficiency, or chronic hypoglycemia, hypoglycemia in these conditions should be treated with glucose.

Information for Patients

Refer patients and family members to the attached Information for the User for instructions describing the method of preparing and injecting glucagon. Advise the patient and family members to become familiar with the technique of preparing glucagon before an emergency arises. Instruct patients to use 1 mg for adults and 1/2 the adult dose (0.5 mg) for pediatric patients weighing less than 44 lb (20 kg).

Patients and family members should be informed of the following measures to prevent hypoglycemic reactions due to insulin:

Reasonable uniformity from day to day with regard to diet, insulin, and exercise.
Careful adjustment of the insulin program so that the type (or types) of insulin, dose, and time (or times) of administration are suited to the individual patient.
Frequent testing of the blood or urine for glucose so that a change in insulin requirements can be foreseen.
Routine carrying of sugar, candy, or other readily absorbable carbohydrate by the patient so that it may be taken at the first warning of an oncoming reaction.

To prevent severe hypoglycemia, patients and family members should be informed of the symptoms of mild hypoglycemia and how to treat it appropriately.

Family members should be informed to arouse the patient as quickly as possible because prolonged hypoglycemia may result in damage to the central nervous system. Glucagon or intravenous glucose should awaken the patient sufficiently so that oral carbohydrates may be taken.

Patients should be advised to inform their physician when hypoglycemic reactions occur so that the treatment regimen may be adjusted if necessary.

Laboratory Tests

Blood glucose determinations should be obtained to follow the patient with hypoglycemia until patient is asymptomatic.

Carcinogenesis, Mutagenesis, Impairment of Fertility

Because glucagon is usually given in a single dose and has a very short half-life, no studies have been done regarding carcinogenesis. In a series of studies examining effects on the bacterial mutagenesis (Ames) assay, it was determined that an increase in colony counts was related to technical difficulties in running this assay with peptides and was not due to mutagenic activities of the glucagon.

Reproduction studies have been performed in rats at doses up to 2 mg/kg glucagon administered two times a day (up to 40 times the human dose based on body surface area, mg/m2) and have revealed no evidence of impaired fertility.

Pregnancy

Reproduction studies have not been performed with recombinant glucagon. However, studies with animal-sourced glucagon were performed in rats at doses up to 2 mg/kg glucagon administered two times a day (up to 40 times the human dose based on body surface area, mg/m2), and have revealed no evidence of impaired fertility or harm to the fetus due to glucagon. There are, however, no adequate and well-controlled studies in pregnant women. Because animal reproduction studies are not always predictive of human response, this drug should be used during pregnancy only if clearly needed.

Nursing Mothers

It is not known whether this drug is excreted in human milk. Because many drugs are excreted in human milk, caution should be exercised when glucagon is administered to a nursing woman. If the drug is excreted in human milk during its short half-life, it will be hydrolyzed and absorbed like any other polypeptide. Glucagon is not active when taken orally because it is destroyed in the gastrointestinal tract before it can be absorbed.

Pediatric Use

For the treatment of severe hypoglycemia: The use of glucagon in pediatric patients has been reported to be safe and effective.2-6

For use as a diagnostic aid: Effectiveness has not been established in pediatric patients.

Geriatric Use

Clinical studies of glucagon did not include sufficient numbers of subjects aged 65 and over to determine whether they respond differently from younger subjects. Other reported clinical experience has not identified differences in responses between the elderly and younger patients. In general, dose selection for an elderly patient should be cautious, usually starting at the low end of the dosing range, reflecting the greater frequency of decreased hepatic, renal, or cardiac function, and of concomitant disease or other drug therapy.

ADVERSE REACTIONS

Side effects may include nausea and vomiting. These reactions may also occur with hypoglycemia. Generalized allergic reactions have been reported (see WARNINGS). In a three month controlled study of 75 volunteers comparing animal-sourced glucagon with glucagon manufactured through rDNA technology, no glucagon-specific antibodies were detected in either treatment group.

Necrolytic migratory erythema (NME) cases have been reported postmarketing in patients receiving continuous infusions of glucagon (see WARNINGS).

OVERDOSAGE

Signs and Symptoms — If overdosage occurs, nausea, vomiting, gastric hypotonicity, and diarrhea would be expected without causing consequential toxicity.

Intravenous administration of glucagon has been shown to have positive inotropic and chronotropic effects. A transient increase in both blood pressure and pulse rate may occur following the administration of glucagon. Patients taking β-blockers might be expected to have a greater increase in both pulse and blood pressure, an increase of which will be transient because of glucagon's short half-life. The increase in blood pressure and pulse rate may require therapy in patients with pheochromocytoma or coronary artery disease.

When glucagon was given in large doses to patients with cardiac disease, investigators reported a positive inotropic effect. These investigators administered glucagon in doses of 0.5 to 16 mg/hour by continuous infusion for periods of 5 to 166 hours. Total doses ranged from 25 to 996 mg, and a 21-month-old infant received approximately 8.25 mg in 165 hours. Side effects included nausea, vomiting, and decreasing serum potassium concentration. Serum potassium concentration could be maintained within normal limits with supplemental potassium.

The intravenous median lethal dose for glucagon in mice and rats is approximately 300 mg/kg and 38.6 mg/kg, respectively.

Because glucagon is a polypeptide, it would be rapidly destroyed in the gastrointestinal tract if it were to be accidentally ingested.

Treatment — To obtain up-to-date information about the treatment of overdose, a good resource is your certified Regional Poison Control Center. Telephone numbers of certified poison control centers are listed in the Physicians' Desk Reference (PDR). In managing overdosage, consider the possibility of multiple drug overdoses, interaction among drugs, and unusual drug kinetics in your patient.

In view of the extremely short half-life of glucagon and its prompt destruction and excretion, the treatment of overdosage is symptomatic, primarily for nausea, vomiting, and possible hypokalemia.

If the patient develops a dramatic increase in blood pressure, 5 to 10 mg of phentolamine mesylate has been shown to be effective in lowering blood pressure for the short time that control would be needed.

Forced diuresis, peritoneal dialysis, hemodialysis, or charcoal hemoperfusion have not been established as beneficial for an overdose of glucagon.

DOSAGE & ADMINISTRATION

General Instructions for Use:

The diluent is provided for use only in the preparation of glucagon for parenteral injection and for no other use.
Glucagon should not be used at concentrations greater than 1 mg/mL.
Reconstituted glucagon should be used immediately. Discard any unused portion.
Reconstituted glucagon solutions should be used only if they are clear and of a water-like consistency.
Parenteral drug products should be inspected visually for particulate matter and discoloration prior to administration.

Directions for Treatment of Severe Hypoglycemia:

Severe hypoglycemia should be treated initially with intravenous glucose, if possible.

If parenteral glucose can not be used, dissolve the lyophilized glucagon using the accompanying diluting solution and use immediately.
For adults and for pediatric patients weighing more than 44 lb (20 kg), give 1 mg by subcutaneous, intramuscular, or intravenous injection.
For pediatric patients weighing less than 44 lb (20 kg), give 0.5 mg or a dose equivalent to 20 to 30 mcg/kg.2-6
Discard any unused portion.
An unconscious patient will usually awaken within 15 minutes following the glucagon injection. If the response is delayed, there is no contraindication to the administration of an additional dose of glucagon; however, in view of the deleterious effects of cerebral hypoglycemia emergency aid should be sought so that parenteral glucose can be given.
After the patient responds, supplemental carbohydrate should be given to restore liver glycogen and to prevent secondary hypoglycemia.

Directions for Use as a Diagnostic Aid:

Dissolve the lyophilized glucagon using the accompanying diluting solution and use immediately. Discard any unused portion.

The doses in the following table may be administered for relaxation of the stomach, duodenum, and small bowel, depending on the onset and duration of effect required for the examination. Since the stomach is less sensitive to the effect of glucagon, 0.5 mg intravenous or 2 mg intramuscular are recommended.

* Administration of 2 mg doses produces a higher incidence of nausea and vomiting than do lower doses.

For examination of the colon, it is recommended that a 2 mg dose be administered intramuscularly approximately 10 minutes prior to the procedure. Colon relaxation and reduction of patient discomfort may allow the radiologist to perform a more satisfactory examination.

HOW SUPPLIED

GLUCAGEN(R) {GLUCAGON (rDNA ORGIN) FOR INJECTION} is supplied in the following dosage forms.
NDC 51662-1323-1
GLUCAGEN(R) {GLUCAGON (rDNA ORGIN) FOR INJECTION} 1mg PER KIT

HF Acquisition Co LLC, DBA HealthFirst
Mukilteo, WA 98275

Also supplied in the following manufacture supplied dosage forms

Glucagon Emergency Kit for Low Blood Sugar (NDC 0002-8031-01) contains 1 mg glucagon for injection (as a sterile, lyophilized white to off-white powder) in a single-dose vial and 1 mL of diluent for glucagon in a prefilled syringe.

Stability and Storage:

Before Reconstitution — Vials of glucagon, as well as the diluent for glucagon, may be stored at controlled room temperature 20° to 25°C (68° to 77°F)[see USP].

The USP defines controlled room temperature by the following: A temperature maintained thermostatically that encompasses the usual and customary working environment of 20° to 25°C (68° to 77°F); that results in a mean kinetic temperature calculated to be not more than 25°C; and that allows for excursions between 15° and 30°C (59° and 86°F) that are experienced in pharmacies, hospitals, and warehouses.

After Reconstitution — Glucagon for Injection should be used immediately. Discard any unused portion.

REFERENCES

Drug Information for the Health Care Professional. 18th ed. Rockville, Maryland: The United States Pharmacopeial Convention, Inc; 1998; I:1512.
Gibbs et al: Use of glucagon to terminate insulin reactions in diabetic children. Nebr Med J 1958;43:56-57.
Cornblath M, et al: Studies of carbohydrate metabolism in the newborn: Effect of glucagon on concentration of sugar in capillary blood of newborn infant. Pediatrics 1958;21:885-892.
Carson MJ, Koch R: Clinical studies with glucagon in children. J Pediatr 1955;47:161-170.
Shipp JC, et al: Treatment of insulin hypoglycemia in diabetic campers. Diabetes 1964;13:645-648.
Aman J, Wranne L: Hypoglycemia in childhood diabetes II: Effect of subcutaneous or intramuscular injection of different doses of glucagon. Acta Pediatr Scand 1988;77:548-553.

SPL UNCLASSIFIED

Literature revised July 2018

Marketed by: Lilly USA, LLC
Indianapolis, IN 46285, USA

Copyright © 1999, 2018, Eli Lilly and Company. All rights reserved.

GLU-0003-USPI-20180706

INFORMATION FOR THE USER

GLUCAGON
FOR INJECTION

BECOME FAMILIAR WITH THE FOLLOWING INSTRUCTIONS BEFORE AN EMERGENCY ARISES. DO NOT USE THIS KIT AFTER DATE STAMPED ON THE VIAL OF GLUCAGON. IF YOU HAVE QUESTIONS CONCERNING THE USE OF THIS PRODUCT, CONSULT A DOCTOR, NURSE OR PHARMACIST.

Make sure that your relatives or close friends know that if you become unconscious, medical assistance must always be sought. Glucagon may have been prescribed so that members of your household can give the injection if you become severely hypoglycemic and are unable to take sugar by mouth. If you are unconscious, glucagon can be given while awaiting medical assistance.

Show your family members and others where you keep this kit and how to use it. They need to know how to use it before you need it. They can practice giving a shot by giving you your normal insulin shots. It is important that they practice. A person who has never given a shot probably will not be able to do it in an emergency.

IMPORTANT

Act quickly. Prolonged unconsciousness may be harmful.
These simple instructions will help you give glucagon successfully.
Turn patient on his/her side to prevent patient from choking.
The contents of the syringe are inactive. You must mix the contents of the syringe with the glucagon in the accompanying bottle before giving injection. (See DIRECTIONS FOR USE below.)
Do not prepare Glucagon for Injection until you are ready to use it.

WARNING: THE PATIENT MAY BE IN A COMA FROM SEVERE HYPERGLYCEMIA (VERY HIGH BLOOD GLUCOSE) RATHER THAN SEVERE HYPOGLYCEMIA (VERY LOW BLOOD SUGAR). IN SUCH A CASE, THE PATIENT WILL NOT RESPOND TO GLUCAGON AND REQUIRES IMMEDIATE MEDICAL ATTENTION.

INDICATIONS FOR USE

Use glucagon to treat insulin coma or insulin reaction resulting from severe hypoglycemia (very low blood sugar). Symptoms of severe hypoglycemia include disorientation, unconsciousness, and seizures or convulsions. Give glucagon if (1) the patient is unconscious (2) the patient is unable to eat sugar or a sugar-sweetened product (3) the patient is having a seizure, or (4) repeated administration of sugar or a sugar-sweetened product such as a regular soft drink or fruit juice does not improve the patient's condition. Milder cases of hypoglycemia should be treated promptly by eating sugar or a sugar-sweetened product. (See INFORMATION ON HYPOGLYCEMIA below for more information on the symptoms of hypoglycemia.) Glucagon is not active when taken orally.

DIRECTIONS FOR USE

TO PREPARE GLUCAGON FOR INJECTION

Remove the flip-off seal from the bottle of glucagon. Wipe rubber stopper on bottle with alcohol swab.

2. Remove the needle protector from the syringe, and inject the entire contents of the syringe into the bottle of glucagon. DO NOT REMOVE THE PLASTIC CLIP FROM THE SYRINGE. Remove syringe from the bottle.

3. Swirl bottle gently until glucagon dissolves completely. GLUCAGON SHOULD NOT BE USED UNLESS THE SOLUTION IS CLEAR AND OF A WATER-LIKE CONSISTENCY.

TO INJECT GLUCAGON

Use Same Technique as for Injecting Insulin

4. Using the same syringe, hold bottle upside down and, making sure the needle tip remains in solution, gently withdraw all of the solution (1 mg mark on syringe) from bottle. The plastic clip on the syringe will prevent the rubber stopper from being pulled out of the syringe; however, if the plastic plunger rod separates from the rubber stopper, simply reinsert the rod by turning it clockwise. The usual adult dose is 1 mg. For children weighing less than 44 lb (20 kg), give 1/2 adult dose (0.5 mg). For children, withdraw 1/2 of the solution from the bottle (0.5 mg mark on syringe). DISCARD UNUSED PORTION.

USING THE FOLLOWING DIRECTIONS, INJECT GLUCAGON IMMEDIATELY AFTER MIXING.

Cleanse injection site on buttock, arm, or thigh with alcohol swab.
Insert the needle into the loose tissue under the cleansed injection site, and inject all (or 1/2 for children weighing less than 44 lb) of the glucagon solution. Apply light pressure at the injection site, and withdraw the needle. Press an alcohol swab against the injection site.
Turn the patient on his/her side. When an unconscious person awakens, he/she may vomit. Turning the patient on his/her side will prevent him/her from choking.
FEED THE PATIENT AS SOON AS HE/SHE AWAKENS AND IS ABLE TO SWALLOW. Give the patient a fast-acting source of sugar (such as a regular soft drink or fruit juice) and a long-acting source of sugar (such as crackers and cheese or a meat sandwich). If the patient does not awaken within 15 minutes, give another dose of glucagon and INFORM A DOCTOR OR EMERGENCY SERVICES IMMEDIATELY.
Even if the glucagon revives the patient, his/her doctor should be promptly notified. A doctor should be notified whenever severe hypoglycemic reactions occur.

INFORMATION ON HYPOGLYCEMIA

Early symptoms of hypoglycemia (low blood glucose) include:

If not treated, the patient may progress to severe hypoglycemia that can include:

The occurrence of early symptoms calls for prompt and, if necessary, repeated administration of some form of carbohydrate. Patients should always carry a quick source of sugar, such as candy mints or glucose tablets. The prompt treatment of mild hypoglycemic symptoms can prevent severe hypoglycemic reactions. If the patient does not improve or if administration of carbohydrate is impossible, glucagon should be given or the patient should be treated with intravenous glucose at a medical facility. Glucagon, a naturally occurring substance produced by the pancreas, is helpful because it enables the patient to produce his/her own blood glucose to correct the hypoglycemia.

POSSIBLE PROBLEMS WITH GLUCAGON TREATMENT

Side effects may include nausea and vomiting, a temporary increase in heart rate, and allergic reactions to glucagon or to one of the inactive ingredients in glucagon.

If you experience any other reactions which are likely to have been caused by glucagon, please contact your doctor.

STORAGE

Store the kit at controlled room temperature between 20° to 25°C (68° to 77°F) before mixing glucagon with the diluent.

Glucagon that has been mixed with diluent should be used immediately. Discard any unused portion. Solutions should be clear and of a water-like consistency at time of use.

Literature revised April 2018

Marketed by: Lilly USA, LLC
Indianapolis, IN 46285, USA

Copyright © 1999, 2018, Eli Lilly and Company. All rights reserved.

GLU-0002-PPI-20180418

PACKAGE LABEL, GLUCAGON 1 MG EMERGENCY KIT 1CT

Lilly

Rx only

Glucagon Emergency Kit for Low Blood Sugar

Glucagon for Injection 1 mg (1 unit)

NDC 0002-8031-01

MS8031

Marketed by: Lilly USA, LLC

Indianapolis, IN 46285, USA

Glucagon: Product of Austria

Diluting Syringe: Product of Germany